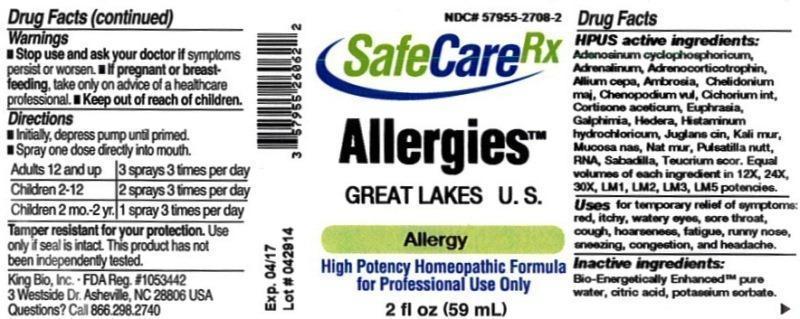 DRUG LABEL: Allergies Great Lakes U.S.
NDC: 57955-2708 | Form: LIQUID
Manufacturer: King Bio Inc.
Category: homeopathic | Type: HUMAN OTC DRUG LABEL
Date: 20140620

ACTIVE INGREDIENTS: ADENOSINE CYCLIC PHOSPHATE 12 [hp_X]/59 mL; EPINEPHRINE 12 [hp_X]/59 mL; CORTICOTROPIN 12 [hp_X]/59 mL; ONION 12 [hp_X]/59 mL; AMBROSIA ARTEMISIIFOLIA 12 [hp_X]/59 mL; CHELIDONIUM MAJUS 12 [hp_X]/59 mL; CHENOPODIUM VULVARIA 12 [hp_X]/59 mL; CHICORY ROOT 12 [hp_X]/59 mL; CORTISONE ACETATE 12 [hp_X]/59 mL; EUPHRASIA STRICTA 12 [hp_X]/59 mL; GALPHIMIA GLAUCA FLOWERING TOP 12 [hp_X]/59 mL; HEDERA HELIX FLOWERING TWIG 12 [hp_X]/59 mL; HISTAMINE DIHYDROCHLORIDE 12 [hp_X]/59 mL; JUGLANS CINEREA BRANCH BARK/ROOT BARK 12 [hp_X]/59 mL; POTASSIUM CHLORIDE 12 [hp_X]/59 mL; SUS SCROFA NASAL MUCOSA 12 [hp_X]/59 mL; SODIUM CHLORIDE 12 [hp_X]/59 mL; ANEMONE PATENS 12 [hp_X]/59 mL; SACCHAROMYCES CEREVISIAE RNA 12 [hp_X]/59 mL; SCHOENOCAULON OFFICINALE SEED 12 [hp_X]/59 mL; TEUCRIUM SCORODONIA FLOWERING TOP 12 [hp_X]/59 mL
INACTIVE INGREDIENTS: WATER; CITRIC ACID MONOHYDRATE; POTASSIUM SORBATE

Allergies™ Great Lakes U.S.

ACTIVE INGREDIENT

Drug Facts__________________________________________________________________________________________________________

HPUS active ingredients: Adenosinum cyclophosphoricum, Adrenalinum, Adrenocorticotrophin, Allium cepa, Ambrosia artemisiaefolia, Chelidonium majus, Chenopodium vulvaria, Cichorium intybus, Cortisone aceticum, Euphrasia officinalis, Galphimia glauca, Hedera helix, Histaminum hydrochloricum, Juglans cinerea, Kali muriaticum, Mucosa nasalis suis, Natrum muriaticum, Pulsatilla nuttalliana, RNA, Sabadilla, Teucrium scorodonia. Equal volumes of each ingredient in 12X, 24X, 30X, LM1, LM2, LM3, LM5 potencies.

INDICATIONS AND USAGE

Uses for temporary relief of symptoms: red, itchy, watery eyes, sore throat, cough, hoarseness, fatigue, runny nose, sneezing, congestion, and headache.

Inactive Ingredients:

Bio-Energetically Enhanced™ pure water, citric acid and potassium sorbate.

Warnings

- Stop use and ask your doctor if symptoms persist or worsen.
- If pregnant or breast-feeding, take only on advice of a healthcare professional.

- Keep out of reach of children.

Directions

- Initially, depress pump until primed.
- Spray one dose directly into mouth.
- Adults 12 and up: 3 sprays 3 times per day.
- Children 2-12: 2 sprays 3 times per day.
- Children 2 mo-2 yr: 1 spray 3 times per day.

OTHER SAFETY INFORMATION

Tamper resistant for your protection. Use only if seal is intact. This product has not been independently tested.

PURPOSE

Uses for temporary relief of symptoms:

- red, itchy, watery eyes
- sore throat
- cough
- hoarseness
- fatigue
- runny nose
- sneezing
- congestion
- headache